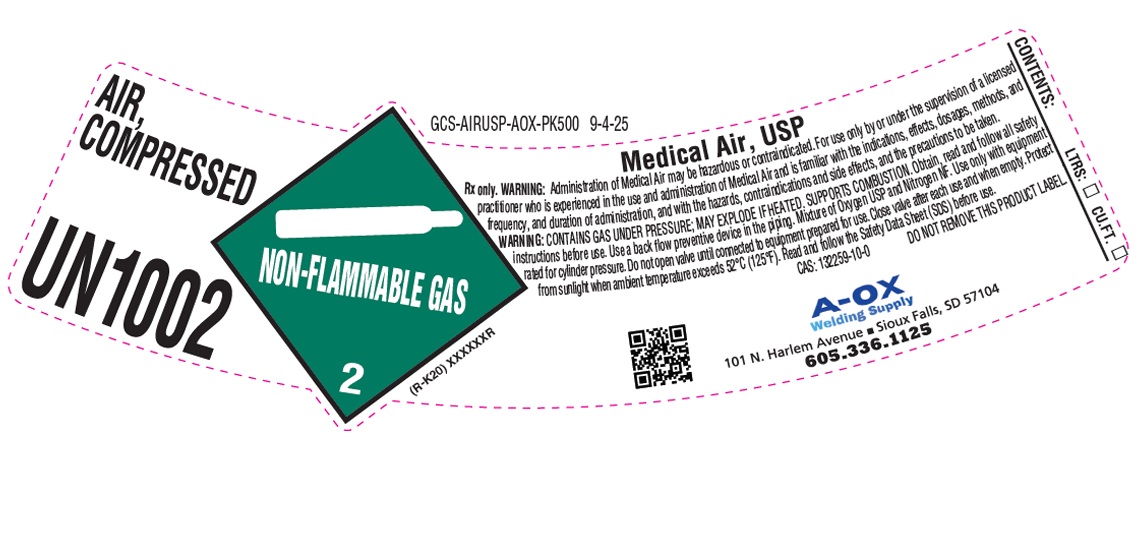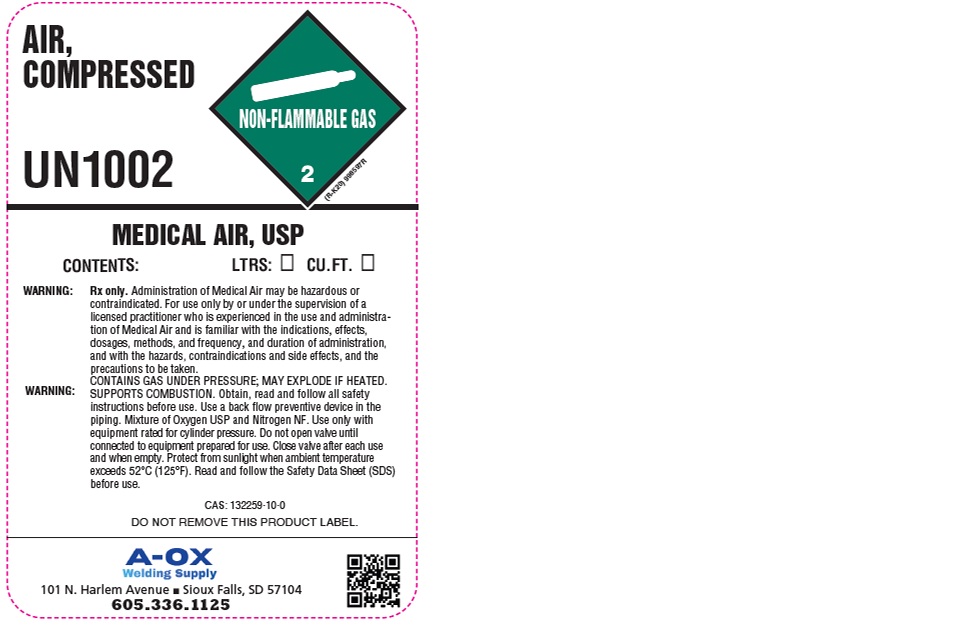 DRUG LABEL: Air
NDC: 10297-013 | Form: GAS
Manufacturer: A-OX Welding Supply, LLC
Category: animal | Type: PRESCRIPTION ANIMAL DRUG LABEL
Date: 20251111

ACTIVE INGREDIENTS: AIR 1000 mL/1 L

Air

PACKAGE LABEL

AIR, COMPRESSED
UN1022
Medical Air, USP
Rx only. WARNING: Administration of Medical Air may be hazardous or contraindicated. For use only by or under the supervision of a licensed practitioner who is experienced in the use of administration of Medical Air and is familiar with the indications, effects, dosages, methods, and frequency, and duration of administration, and with the hazards, contraindications and side effects, and the precautions to be taken.
WARNING: CONTAINS GAS UNDER PRESSURE; MAY EXPLODE IF HEATED. SUPPORT COMBUSTION. Obtain, read and follow all safety instructions before use. Use a back flow preventive device in the piping. Mixture of Oxygen USP and Nitrogen NF. Use only with equipment rated for cylinder pressure. Do no open valve until connected to equipment prepared for use. Close valve after each use and when empty. Protect from sunlight when ambient temperature exceeds 52 C (125 F). Read and follow the Safety Data Sheet (SDS) before use.
CAS: 132259-10-0 DO NOT REMOVE THIS PRODUCT LABEL.
CONTENTS: LTRS: CU.FT.
A-OX Welding Supply
101 N. Harlem Avenue Sioux Falls, SD 57104
605.336.1125

PACKAGE LABEL

AIR, COMPRESSED
UN1002
MEDICAL AIR, USP
CONTENTS: LTRS: CU.FT.
WARNING: Rx only. Administration of Medical Air may be hazardous or contraindicated. For use only by or under the supervision of a licensed practitioner who is experienced in the use and administration of Medical Air and is familiar with the indications, effects, dosages, methods, and frequency, and duration of administration, and with the hazards, contraindications and side effects, and the precautions to be taken.
WARNING: CONTAINS GAS UNDER PRESSURE; MAY EXPLODE IF HEATED. SUPPORTS COMBUSTION. Obtain, read and follow all safety instructions before use. Use a back flow preventive device in the piping. Mixture of Oxygen USP and Nitrogen NF. Use only with equipment rated for cylinder pressure. Do not open valve until connected to equipment prepared for use. Close valve after each use and when empty. Protect from sunlight when ambient temperature exceeds 52 C (125 F). Read and follow the Safety Data Sheet (SDS) before use.
CAS: 132259-10-0
DO NOT REMOVE THIS PRODUCT LABEL.
A-OX Welding Supply
101 N. Harlem Avenue Sioux Falls, SD 57104
605.336.1125